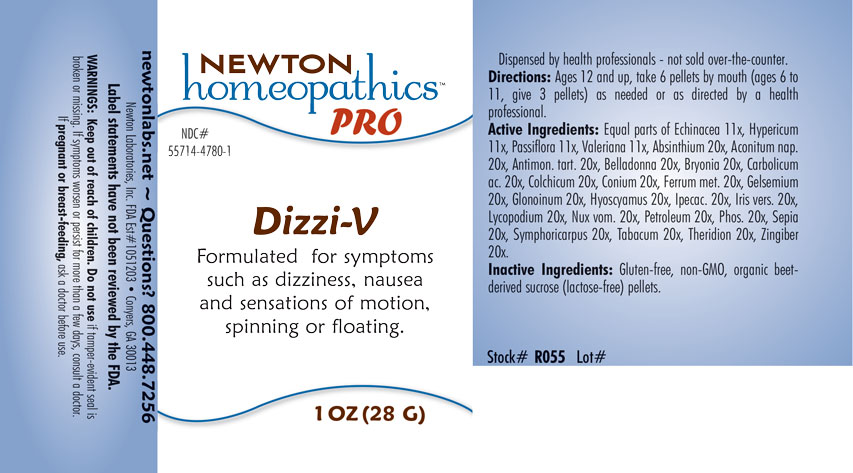 DRUG LABEL: Dizzi-V
NDC: 55714-4780 | Form: PELLET
Manufacturer: Newton Laboratories, Inc.
Category: homeopathic | Type: HUMAN OTC DRUG LABEL
Date: 20201202

ACTIVE INGREDIENTS: WORMWOOD 20 [hp_X]/1 g; ACONITUM NAPELLUS 20 [hp_X]/1 g; ANTIMONY POTASSIUM TARTRATE 20 [hp_X]/1 g; ATROPA BELLADONNA 20 [hp_X]/1 g; BRYONIA ALBA ROOT 20 [hp_X]/1 g; PHENOL 20 [hp_X]/1 g; COLCHICUM AUTUMNALE BULB 20 [hp_X]/1 g; CONIUM MACULATUM FLOWERING TOP 20 [hp_X]/1 g; IRON 20 [hp_X]/1 g; GELSEMIUM SEMPERVIRENS ROOT 20 [hp_X]/1 g; NITROGLYCERIN 20 [hp_X]/1 g; HYOSCYAMUS NIGER 20 [hp_X]/1 g; IPECAC 20 [hp_X]/1 g; IRIS VERSICOLOR ROOT 20 [hp_X]/1 g; LYCOPODIUM CLAVATUM SPORE 20 [hp_X]/1 g; STRYCHNOS NUX-VOMICA SEED 20 [hp_X]/1 g; KEROSENE 20 [hp_X]/1 g; PHOSPHORUS 20 [hp_X]/1 g; SEPIA OFFICINALIS JUICE 20 [hp_X]/1 g; SYMPHORICARPOS ALBUS FRUIT 20 [hp_X]/1 g; TOBACCO LEAF 20 [hp_X]/1 g; THERIDION CURASSAVICUM 20 [hp_X]/1 g; GINGER 20 [hp_X]/1 g; ECHINACEA, UNSPECIFIED 11 [hp_X]/1 g; HYPERICUM PERFORATUM 11 [hp_X]/1 g; PASSIFLORA INCARNATA FLOWERING TOP 11 [hp_X]/1 g; VALERIAN 11 [hp_X]/1 g
INACTIVE INGREDIENTS: SUCROSE

Dizzi-V 4780P

INDICATIONS & USAGE SECTION

Formulated for symptoms such as dizziness, nausea and sensations of motion, spinning or floating.

DOSAGE & ADMINISTRATION SECTION

Directions: Ages 12 and up, take 6 pellets by mouth (ages 0 to 11, give 3 pellets) as needed or as directed by a health professional.

OTC - ACTIVE INGREDIENT SECTION

Equal parts of Echinacea 11x, Hypericum perforatum 11x, Passiflora incarnata 11x, Valeriana officinalis 11x, Absinthium 20x, Aconitum napellus 20x, Antimonium tartaricum 20x, Belladonna 20x, Bryonia 20x, Carbolicum acidum 20x, Colchicum autumnale 20x, Conium maculatum 20x, Ferrum metallicum 20x, Gelsemium sempervirens 20x, Glonoinum 20x, Hyoscyamus niger 20x, Ipecacuanha 20x, Iris versicolor 20x, Lycopodium clavatum 20x, Nux vomica 20x, Petroleum 20x, Phosphorus 20x, Sepia 20x, Symphoricarpus racemosus 20x, Tabacum 20x, Theridion 20x, Zingiber officinale 20x.

OTC - PURPOSE SECTION

Formulated for symptoms such as dizziness, nausea and sensations of motion, spinning or floating.

INACTIVE INGREDIENT SECTION

Inactive Ingredients: Gluten-free, non-GMO, organic beet-drived sucrose (lactose-free) pellets.

QUESTIONS SECTION

newtonlabs.net – Questions? 800.448.7256

Newton Laboratories, Inc. FDA Est # 1051203 - Conyers, GA 30013

WARNINGS SECTION

WARNINGS: Keep out of reach of children. Do not use if tamper-evident seal is broken or missing. If symptoms worsen or persist for more than a few days, consult a doctor. If pregnant or breast-feeding, ask a doctor before use.

OTC - PREGNANCY OR BREAST FEEDING SECTION

If pregnant or breast-feeding, ask a doctor before use.

OTC - KEEP OUT OF REACH OF CHILDREN SECTION

Keep out of reach of children.